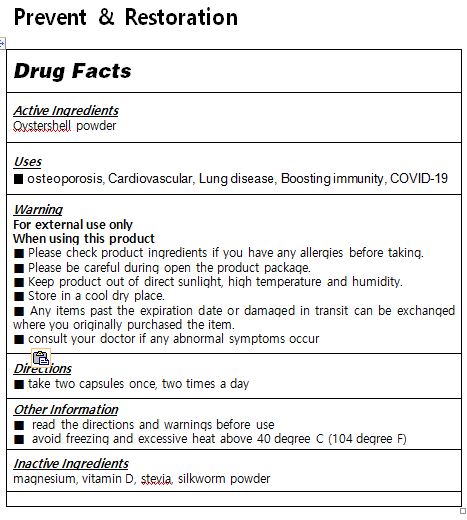 DRUG LABEL: Prevent Restoration
NDC: 55259-1191 | Form: TABLET
Manufacturer: APEXEL CO., LTD.
Category: otc | Type: HUMAN OTC DRUG LABEL
Date: 20240123

ACTIVE INGREDIENTS: OSTREA EDULIS SHELL 0.67 mg/1 1
INACTIVE INGREDIENTS: VITAMIN D; MAGNESIUM OXIDE; STEVIA LEAF

ACTIVE INGREDIENT

oystershell powder

INACTIVE INGREDIENT

magnesium, vitamin D, stevia

PURPOSE

osteoporosis
Cardiovascular
Lung disease
Boosting immunity
COVID-19

KEEP OUT OF REACH OF CHILDREN

WARNING

Please check product ingredients if you have any allergies before taking.

Please be careful during open the product package.

Keep product out of direct sunlight, high temperature and humidity.

Store in a cool dry place.

Any items past the expiration date or damaged in transit can be exchanged where you originally purchased the item.

consult your doctor if any abnormal symptoms occur

USES

for oral use only

INDICATION & USAGE SECTION

take two capsules once, two times a day